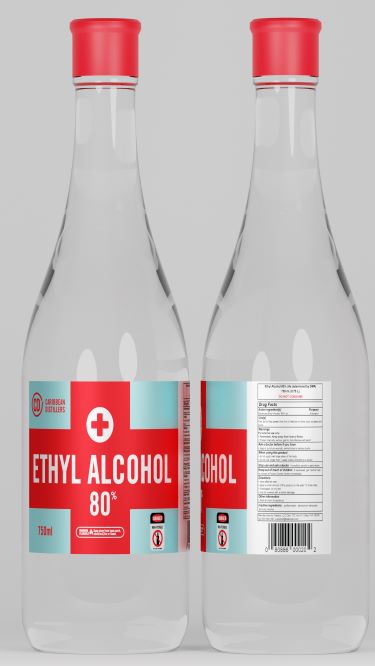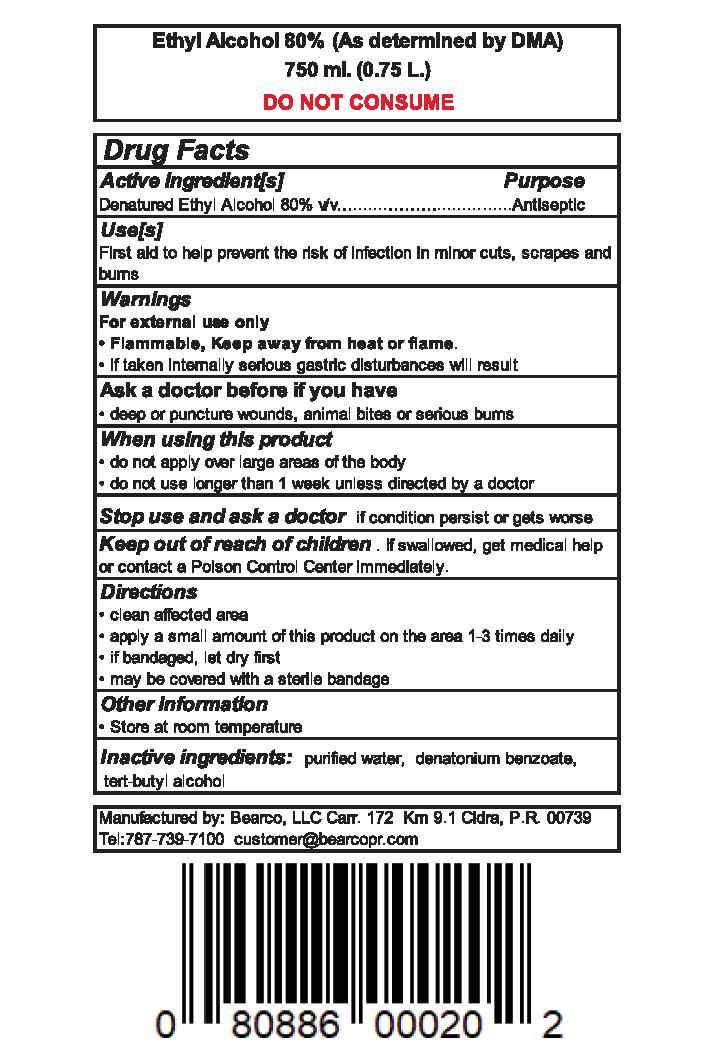 DRUG LABEL: ETHYL ALCOHOL 80 PERCENT
NDC: 74331-800 | Form: LIQUID
Manufacturer: BEARCO
Category: otc | Type: HUMAN OTC DRUG LABEL
Date: 20200624

ACTIVE INGREDIENTS: ALCOHOL 80 mL/100 mL
INACTIVE INGREDIENTS: WATER; DENATONIUM BENZOATE

ETHYL ALCOHOL

PACKAGE LABEL

750 mL NDC 74331-800-01